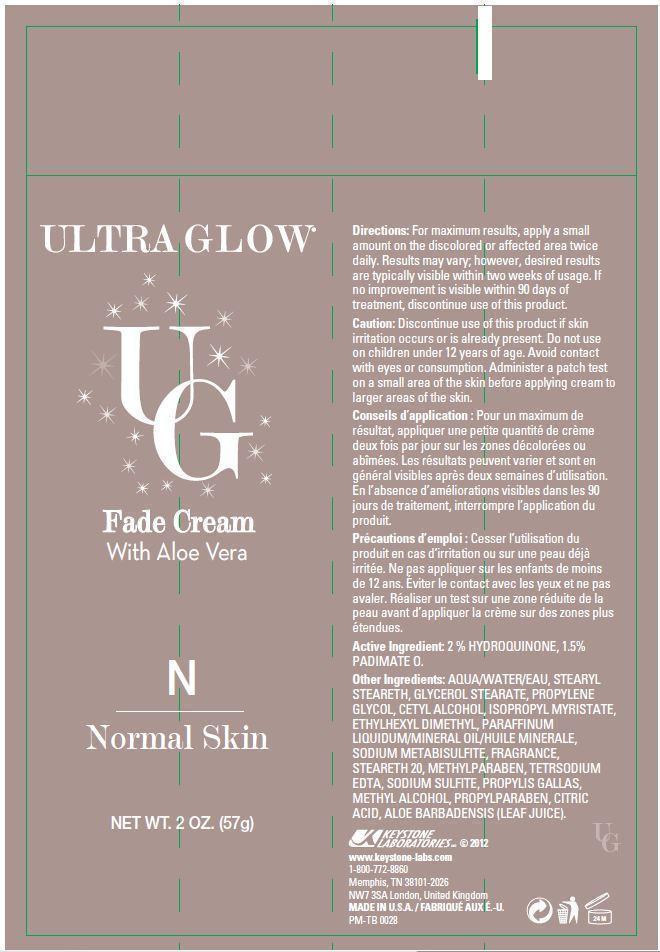 DRUG LABEL: Ultra Glow Fade
NDC: 58318-002 | Form: CREAM
Manufacturer: Keystone Laboratories
Category: otc | Type: HUMAN OTC DRUG LABEL
Date: 20131118

ACTIVE INGREDIENTS: HYDROQUINONE 1 g/57 g; PADIMATE O 1 g/57 g
INACTIVE INGREDIENTS: WATER; GLYCERYL MONOSTEARATE; SODIUM LAURYL SULFATE; PROPYLENE GLYCOL; ISOPROPYL MYRISTATE; CETYL ALCOHOL; SODIUM DITHIONATE; STEARYL STEARATE; STEARETH-20; METHYLPARABEN; PROPYLPARABEN; BUTYLATED HYDROXYTOLUENE; PROPYL GALLATE; SODIUM SULFITE; EDETATE DISODIUM; CITRIC ACID MONOHYDRATE; METHYL ALCOHOL; ALOE VERA LEAF; MINERAL OIL

Active Ingredient: 2% Hydroquinone, 1.5% Padimate O

Keep out of reach of children.

PURPOSE

Skin lightener

INDICATIONS AND USAGE

Ultra Glow Fade Cream with Aloe Vera

WARNINGS

Caution: Discontinue use of this product if skin irritation occurs or is already present. Do not use on children under 12 years of age. Avoid contact with eyes or consumption. Administer a patch test on a small area of the skin before applying cream to larger areas of the skin.

Precautions d'emploi: Cesser l'utilisation du produit en cas d'irritation ou sur une peau deja irritee. Ne pas appliquer sur les enfants de moins de 12 ans. Eviter le contact avec les yeux et ne pas avaler. Realiser un test sur une zone reduite de la peau avand d'appliquer la creme sur des zones plus etendues.

DOSAGE AND ADMINISTRATION

Directions: Apply a small amount on the discolored or affected area twice daily. Results may vary; however, desired results are typically visibile within two weeks of usage. If no improvement is visible within 90 days of treatment, discontinue use of this product.

Conseils d'application: Pour un maximum de resultat, appliquer une petite quantite de creme deux foix par jour sur les zones decolorees ou abimees. Les resultats peuvent varier et sont en general visibles apres deux semaines d'utilisation. En l'absence d'ameliorations visibles dans les 90 jours de traitement, interrompre l'application du produit.

OTHER SAFETY INFORMATION

KEYSTONE LABORATORIES © 2012

www.keystone-labs.com

1-800-772-8860

Memphis, TN 38101-2026

NW7 3SA London, United Kingdom

MADE IN U.S.A. / FABRIQUE AUX E.-U.

PM-TB 0028

INACTIVE INGREDIENT

Other Ingredients:

aqua/water/eau, stearyl steareth, glycerol stearate, propylene glycol, cetyl alcohol, isopropyl myristate, ethylhexyl dimethyl, paraffinum liquidum/mineral oil/huile minerale, sodium metabisulfite, fragrance, steareth 20, methylparaben, tetrsodium edta, sodium sulfite, propylis gallas, methyl alcohol, propylparaben, citric acid, aloe barbadensis (leaf juice).